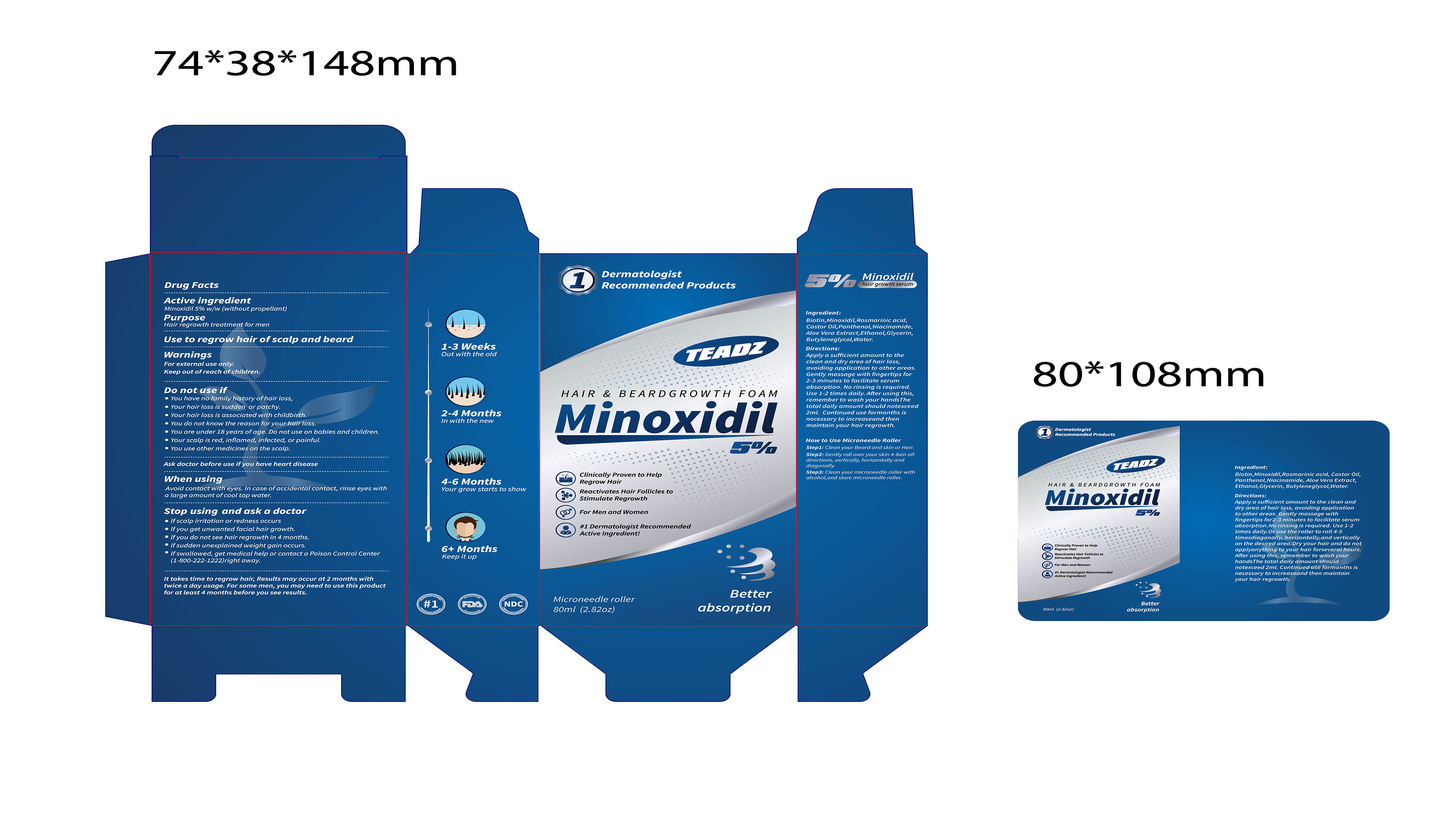 DRUG LABEL: HAIR BEARDGROWTH FOAM
NDC: 85173-001 | Form: LIQUID
Manufacturer: Shenzhen Xuemin E-commerce Co., Ltd.
Category: otc | Type: HUMAN OTC DRUG LABEL
Date: 20250116

ACTIVE INGREDIENTS: MINOXIDIL 5 g/100 mL
INACTIVE INGREDIENTS: BIOTIN; ROSMARINIC ACID; CASTOR OIL; PANTHENOL; NIACINAMIDE; ALOE VERA LEAF; ALCOHOL; GLYCERIN; 1,3-BUTYLENEGLYCOL DIMETHACRYLATE; WATER

HAIR & BEARDGROWTH FOAM

HAIR & BEARDGROWTH FOAM

ACTIVE INGREDIENT

Minoxidil 5%

PURPOSE

Hair regrowth treatment formen

INDICATIONS AND USAGE

Use to regrow hairofscalp and beard

WARNINGS

For externaluse only

Keep out ofreach ofchildren.

DO NOT USE

You have no familyhistoryofhair loss

Your hairloss is sudden or patchy.

Your hair loss is associated with childbirth.

You do not know the reason foryourhair loss.

You are under 18 years ofage. Do not use on babies and children.

Your scalp is red, inflamed, infected, or painful.

You use othermedicines on the scalp.

WHEN USING

Avoid contact with eyes. In case ofaccidental contact, rinse eyes with
a large amount ofcool tap water.

STOP USE

If scalp irritation or redness occurs

If you get unwanted facial hair growth.

lf you do not see hairregrowth in 4 months

If sudden unexplained weight gain occurs.

If swallowed, get medical help orcontact a Poison Control Center(1-800-222-1222)right away.

KEEP OUT OF REACH OF CHILDREN SECTION

DOSAGE AND ADMINISTRATION

Applya sufficient amount to theclean and dry area ofhair loss,avoiding application to other areas,Gently massage with fingertips for2-3 minutes to facilitate serumabsorption. No rinsing is requiredUse 1-2 times daily. After using thisremember to wash your handsThetotaldailyamount should notexceed2ml. Continued use formonths isnecessary to increaseand thenmaintain your hair regrowth.

INACTIVE INGREDIENT

Biotin

Rosmarinic acid

Castor Oil
Panthenol
Niacinamide
Aloe Vera Extract
Ethanol
Glycerin
Butyleneglycol
Water